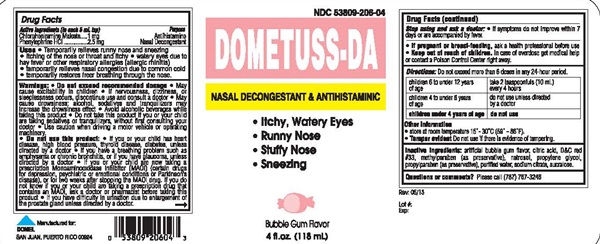 DRUG LABEL: DOMETUSS-DA
NDC: 53809-206 | Form: LIQUID
Manufacturer: Domel Laboratories
Category: otc | Type: HUMAN OTC DRUG LABEL
Date: 20241205

ACTIVE INGREDIENTS: CHLORPHENIRAMINE MALEATE 1 mg/5 mL; PHENYLEPHRINE HYDROCHLORIDE 2.5 mg/5 mL
INACTIVE INGREDIENTS: CITRIC ACID MONOHYDRATE; D&C RED NO. 33; HYDROXYETHYL CELLULOSE (2000 MPA.S AT 1%); METHYLPARABEN; PROPYLENE GLYCOL; PROPYLPARABEN; WATER; SODIUM CITRATE, UNSPECIFIED FORM; SUCRALOSE

DOMETUSS-DA

Drug Facts Active ingredients (in each 5 mL tsp)

Chlorpheniramine Maleate 1 mg

Phenylphrine HCL 2.5 mg

Purpose

Antihistamine

Nasal Decongestant

Keep out of reach of children.

In case of overdose, get medical help or contact a Poison Control Center right away.

Uses

- Temporarily relieves runny nose and sneezing
- itching of the nose or throat and itchy
- watery eyes due to hay fever or other respiratory allergies (allergic rhinitis)
- temporarily relieves nasal congestion due to common cold
- temporarily restores freer breathing through the nose

Warnings

- Do not exceed recommended dosage.
- A persistant cough may be a sign of a serious condition; if cough persists for more than one week, tend to recur, or is accompanied by fever, rash, or persistant headache, consult a doctor.

Do not use this product

- for persistant or chronic cough such as occurs with smoking, asthma, or emphysema, or if cough is accompanied by excessive phlegm (mucus), unless directed by a doctor
- If you are now taking a prescription Monoaminooxidase Inhibitor (MAOI) (certain drugs for depression, psychiatric or emotional conditions or Parkinson's disease), or for two weeks after stopping the MAOI drug; if you do not know if you are taking a prescription drug that contains an MAOI, ask a doctor or pharmacist before taking this product.

If pregnant or breast-feeding

as a health professional before use.

Directions

Do not exceed more than 4 doses in any 24- hour period, or as directed by a physician.

Adults and children 12 years of age and over | Take 1 teaspoonful (5 mL) every 6 hours
Children 6 to under 12 years of age | Take 1/2 teaspoonful (2.5 mL) every 6 hours
Children under 6 years of age | Ask a doctor

Other Information

• store at room temperature 15°-30°C (59°-86°F).

Tamper Evident: Do not use if there is evidence of tampering.

Inactive ingredients

Artificial grape flavor, citric acid, D&C red #33, FD&C blue #1, glycerin, methyl paraben (as preserative), propylene glycol, propyl paraben (as preseratie, purified water, sodium citrate, sucralose.

Questions or comments?

Please call (787) 767-3246

DOMETUSS-DA product label

NDC 53809-206-04

DOMETUSS-DA

NASAL DECONGESTANT & ANTIHISTAMINIC

- Itchy, Waterl Eyes
- Runny Nose
- Stuffy Nose
- Sneezing

bubble gum flavor

4 fl. oz. (118 mL)

Rev: 05/13

Lot #

Exp:

Manufactured for:

DOMEL

SAN JUAN, PUERTO RICO 00924